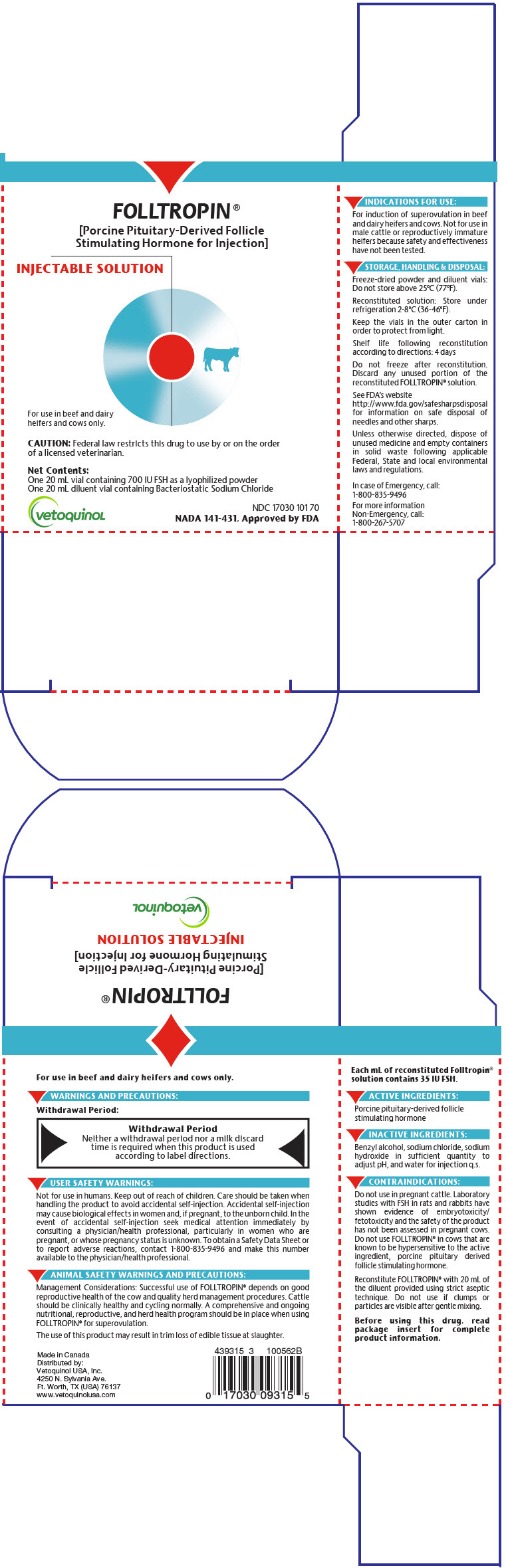 DRUG LABEL: Folltropin
NDC: 17030-101 | Form: KIT | Route: INTRAMUSCULAR
Manufacturer: Vetoquinol USA, Inc.
Category: animal | Type: PRESCRIPTION ANIMAL DRUG LABEL
Date: 20201217

ACTIVE INGREDIENTS: Follicle Stimulating Hormone (Porcine) 700 [iU]/1 1
INACTIVE INGREDIENTS: Sodium Chloride; Benzyl Alcohol; Water

FOLLTROPIN®
[porcine pituitary-derived follicle stimulating hormone for injection]

NADA 141-431, Approved by FDA

CAUTION:

Federal law restricts this drug to use by or on the order of a licensed veterinarian.

DESCRIPTION:

FOLLTROPIN® (porcine pituitary-derived follicle stimulating hormone for injection) is a powder for solution containing 700 IU (equivalent to 400 mg NIH-FSH-P1) of follicle stimulating hormone (FSH) per vial. FOLLTROPIN® contains a low amount of luteinizing hormone (less than 1000 µg NIH-LH-S19 per vial). When reconstituted according to label directions the final solution contains 35 IU FSH per mL for intramuscular injection. There are no inactive ingredients in the FSH vial. A 20 mL vial of sterile diluent for FOLLTROPIN® is supplied containing 9 mg/mL sodium chloride, 18 mg/mL benzyl alcohol, sodium hydroxide in sufficient quantity to adjust pH, and water for injection q.s.

INDICATIONS FOR USE:

For the induction of superovulation in beef and dairy heifers and cows.

Not for use in male cattle or reproductively immature heifers because safety and effectiveness have not been tested.

DOSAGE AND ADMINISTRATION:

For intramuscular injection only.

Reconstitute FOLLTROPIN® with 20 mL of the diluent provided using strict aseptic technique. Do not use if clumps or particles are visible after gentle mixing.

Regimen: Start injections on day 8 to 10 following observed or induced estrus. Administer 2.5 mL (87.5 IU) of FOLLTROPIN® intramuscularly, twice daily at 12 hour intervals, for 4 consecutive days. In conjunction with the 6th dose of FOLLTROPIN®, administer an FDA-approved prostaglandin product (cloprostenol sodium or dinoprost tromethamine) for cattle, using the labeled dosage and administration instructions to cause luteolysis and induce estrus.

Inseminate animals at 12 and 24 hours after the onset of estrus or 60 and 72 hours after prostaglandin treatment. Additional inseminations may be conducted at 12 hour intervals, if indicated.

Collection of embryos is normally started on day 7 following insemination.

CONTRAINDICATIONS:

Do not use in pregnant cattle. Laboratory studies with FSH in rats and rabbits have shown evidence of embryotoxicity/fetotoxicity and the safety of the product has not been assessed in pregnant cows. Do not use FOLLTROPIN® in cows that are known to be hypersensitive to the active ingredient, porcine pituitary-derived follicle stimulating hormone.

WARNINGS AND PRECAUTIONS:

Withdrawal Period:

Withdrawal Period

Neither a withdrawal period nor a milk discard time is required when this product is used according to label directions.

User Safety Warnings:

Not for use in humans. Keep out of reach of children. Care should be taken when handling the product to avoid accidental self-injection. Accidental self-injection may cause biological effects in women and, if pregnant, to the unborn child. In the event of accidental self-injection seek medical attention immediately by consulting a physician/health professional, particularly in women who are pregnant, or whose pregnancy status is unknown. To obtain a Safety Data Sheet or to report adverse reactions, contact 1-800-835-9496 and make this number available to the physician/health professional.

Animal Safety Warnings and Precautions:

Management considerations: Successful use of FOLLTROPIN® depends on good reproductive health of the cow and quality herd management procedures. Cattle should be clinically healthy and cycling normally. A comprehensive and ongoing nutritional, reproductive, and herd health program should be in place when using FOLLTROPIN® for superovulation.

The use of this product may result in trim loss of edible tissue at slaughter.

ADVERSE REACTIONS:

Following superovulation, a delayed return to heat is possible. Use of this product has been associated with a low incidence of hypersensitivity or anaphylactic reactions. If you notice any serious effects or other effects not mentioned in this leaflet, please inform your veterinarian.

TARGET ANIMAL SAFETY:

Existing pharmacology and toxicology information and knowledge gained from the widespread clinical use of FOLLTROPIN® in cattle was sufficient to demonstrate that FOLLTROPIN® is not systemically toxic to the cow and the targets of toxicity in both cattle and other species are limited to the reproductive organs and functions. A field safety study demonstrated that the use of FOLLTROPIN® in accordance with label directions did not produce any reactions at the injection site. A retrospective study of dairy cattle superovulated up to six times at intervals of less than 93 days did not show any adverse effect of repeated superovulation on the yield of transferable embryos. Cows within the superovulation program produced embryos that were successfully transferred into recipient cows and were able to themselves conceive and deliver normal calves. The development of cystic ovaries following treatment with FOLLTROPIN® has been reported; however, these results have not been substantiated by well-controlled studies or through a comprehensive literature review.

EFFECTIVENESS:

The effectiveness of FOLLTROPIN® for the induction of superovulation in beef and dairy heifers and cows was substantiated through a systematic review and meta-analysis which included 2685 superovulation records obtained from twenty clinical studies and one retrospective study. The analysis revealed a high level of variability in the number of transferable embryos obtained between treatment groups; such variability is representative of the expected variation for superovulation programs. The estimated mean number of transferable embryos was 4.5 per study animal and the 95% confidence limits of the mean were 3.5 (lower limit) and 5.6 (upper limit).

STORAGE, HANDLING, AND DISPOSAL:

Freeze-dried powder and diluent vials: Do not store above 25°C (77°F).

Reconstituted solution: Store under refrigeration (2 to 8 °C; 36 to 46°F).

Keep the vials in the outer carton in order to protect from light.

Shelf life following reconstitution according to directions: 4 days

Do not freeze after reconstitution.

Discard any unused portion of the reconstituted FOLLTROPIN® solution.

See FDA's website http://www.fda.gov/safesharpsdisposal for information on safe disposal of needles and other sharps.

Unless otherwise directed, dispose of unused medicine and empty containers in solid waste following applicable Federal, State and local environmental laws and regulations.

HOW SUPPLIED:

FOLLTROPIN® contains one 20 mL vial containing 700 IU [IU = International Units (established by WHO Expert Committee on Biological Standardization in 1986).] FSH as a lyophilized powder and one 20 mL diluent vial containing Bacteriostatic Sodium Chloride.

CONTACT INFORMATION:

Contact Vétoquinol USA, Inc. at 1-800-267-5707 for customer service or to obtain product information, including a SDS. After hours or to report adverse reactions, call 1-800-835-9496.

For additional information about adverse drug experience reporting for animal drugs, contact FDA at 1-888-FDA-VETS or online at http://www.fda.gov/AnimalVeterinary/SafetyHealth.

Made in Canada
Distributed by:
Vétoquinol USA, Inc.
4250 N. Sylvania Ave.
Ft. Worth, TX (USA) 76137
www.vetoquinolusa.com

PRINCIPAL DISPLAY PANEL - Kit Carton

FOLLTROPIN ®
[Porcine Pituitary-Derived Follicle
Stimulating Hormone for Injection]

INJECTABLE SOLUTION

For use in beef and dairy
heifers and cows only.

CAUTION: Federal law restricts this drug to use by or on the order
of a licensed veterinarian.

Net Contents:
One 20 mL vial containing 700 IU FSH as a lyophilized powder
One 20 mL diluent vial containing Bacteriostatic Sodium Chloride

vetoquinoL

NDC 17030 101 70
NADA 141-431, Approved by FDA